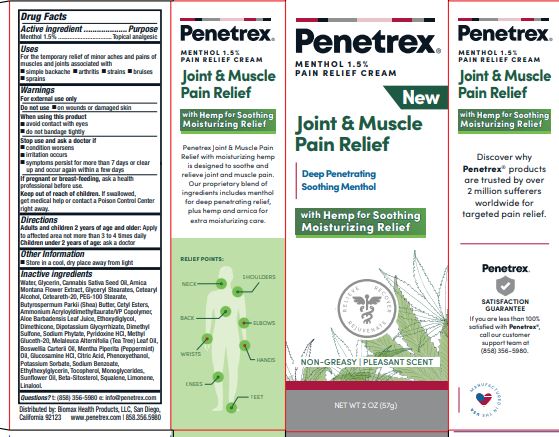 DRUG LABEL: Joint and Muscle Pain Relief
NDC: 62742-4219 | Form: CREAM
Manufacturer: Allure Labs
Category: otc | Type: HUMAN OTC DRUG LABEL
Date: 20241209

ACTIVE INGREDIENTS: MENTHOL 1.5 g/100 g
INACTIVE INGREDIENTS: PYRIDOXINE HYDROCHLORIDE; CITRIC ACID MONOHYDRATE; SODIUM BENZOATE; DIACETYLATED MONOGLYCERIDES; GLYCERIN; CANNABIS SATIVA SEED OIL; ARNICA MONTANA FLOWER; CETOSTEARYL ALCOHOL; POLYOXYL 20 CETOSTEARYL ETHER; PEG-100 STEARATE; SUNFLOWER OIL; SHEA BUTTER; CETYL ESTERS WAX; GLYCERYL MONOSTEARATE; WATER; PEPPERMINT OIL; PHENOXYETHANOL; POTASSIUM SORBATE; TOCOPHEROL; .BETA.-SITOSTEROL; DIETHYLENE GLYCOL MONOETHYL ETHER; DIMETHYL SULFONE; GLUCOSAMINE HYDROCHLORIDE; ETHYLHEXYLGLYCERIN; AMMONIUM ACRYLOYLDIMETHYLTAURATE/VP COPOLYMER; ALOE VERA LEAF; DIMETHICONE; GLYCYRRHIZINATE DIPOTASSIUM; SQUALENE; LINALOOL, (+/-)-; FRANKINCENSE OIL; LIMONENE, (+)-; METHYL GLUCETH-20; TEA TREE OIL

Drug Facts

Active ingredient

Menthol 1.5%

Purpose

Topical analgesic

Uses

For the temporary relief of minor aches and pains of muscles and joints associated with

simple backache

arthritis

strains

bruises

sprains

Warnings

For external use only

Do not use

on wounds or damaged skin

When using this product

avoid contact with eyes

do not bandage tightly

Stop use and ask a doctor if

condition worsens

irritation occurs

symptoms persist for more than 7 days or clear up and occur again within a few days

Keep out of reach of children.

If swallowed, get medical help or contact a Poison Control Center right away.

Directions

Adults and children 2 years of age and olden Apply to affected area not more than 3 to 4 times daily Children under 2 years of age: ask a doctor

Other Information

Store in a cool, dry place away from light

If pregnant or breast-feeding, ask a health professional before use

Inactive Ingredients

Water, Glycerin,Cannabis Sativa Seed Oil, Arnica Montana Flower Extract, Glyceryl Stearates, Cetearyl Alcohol,Ceteareth-20,

PEG-100 Stearate,Butyrospermum Parkii (Shea) Butter, Cetyl Esters,Ammonium Acryloyldimethyltaurate/VP Copolymer,

Aloe Barbadensis Leaf Juice, Ethoxydiglycol, Dimethicone, Dipotassium Glycyrrhizate,Dimethyl Sulfone, Sodium Phytate,

Pyridoxine HCI, Methyl Gluceth-20, Melaleuca Alternifolia (Tea Tree) Leaf Oil, Boswellia Carterii Oil,Menthe Piperita (Peppermint) Oil,Glucosamine HCI, Citric Acid, Phenoxyethanol,Potassium Sorbate,Sodium Benzoate, Ethylhexylglycerin,Tocopherol,

Monoglycerides,Sunflower Oil,Beta-Sitosterol, Squalene,Limonene, Linalool.